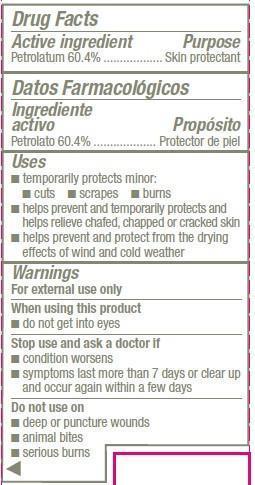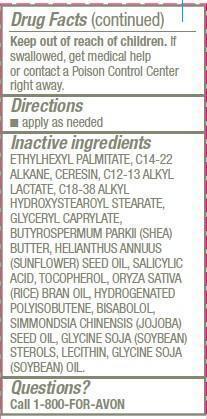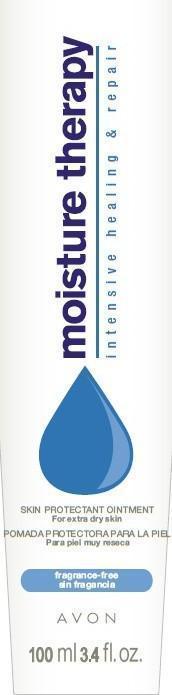 DRUG LABEL: Moisture Therapy
NDC: 10096-0292 | Form: OINTMENT
Manufacturer: New Avon LLC
Category: otc | Type: HUMAN OTC DRUG LABEL
Date: 20160217

ACTIVE INGREDIENTS: Petrolatum 604 mg/1 mL

Active ingredient
Petrolatum 60.4%...........................

Purpose
........................Skin protectant

Uses
• temporarily protects minor:• cuts • scrapes • burns
• helps prevent and temporarily protects and helps relieve chafed, chapped or cracked skin
• helps prevent and protect from the drying effects of wind and cold weather

Warnings
For external use only

When using this product
• do not get into eyes

Stop use and ask a doctor if
• condition worsens
• symptoms last more than 7 days or clear up and occur again within a few days

Do not use on
• deep or puncture wounds
• animal bites
• serious burns

Keep out of reach of children. If swallowed, get medical help or contact a Poison Control Center right away.

Directions
• apply as needed

Inactive ingredients
ETHYLHEXYL PALMITATE, C14-22 ALKANE, CERESIN, C12-13 ALKYL LACTATE, C18-38 ALKYL HYDROXYSTEAROYL STEARATE, GLYCERYL CAPRYLATE, BUTYROSPERMUM PARKII (SHEA) BUTTER, HELIANTHUS ANNUUS (SUNFLOWER) SEED OIL, SALICYLIC ACID, TOCOPHEROL, ORYZA SATIVA (RICE) BRAN OIL, HYDROGENATED POLYISOBUTENE, BISABOLOL, SIMMONDSIA CHINENSIS (JOJOBA) SEED OIL, GLYCINE SOJA (SOYBEAN) STEROLS, LECITHIN, GLYCINE SOJA (SOYBEAN) OIL.

Questions? Call 1-800-FOR-AVON